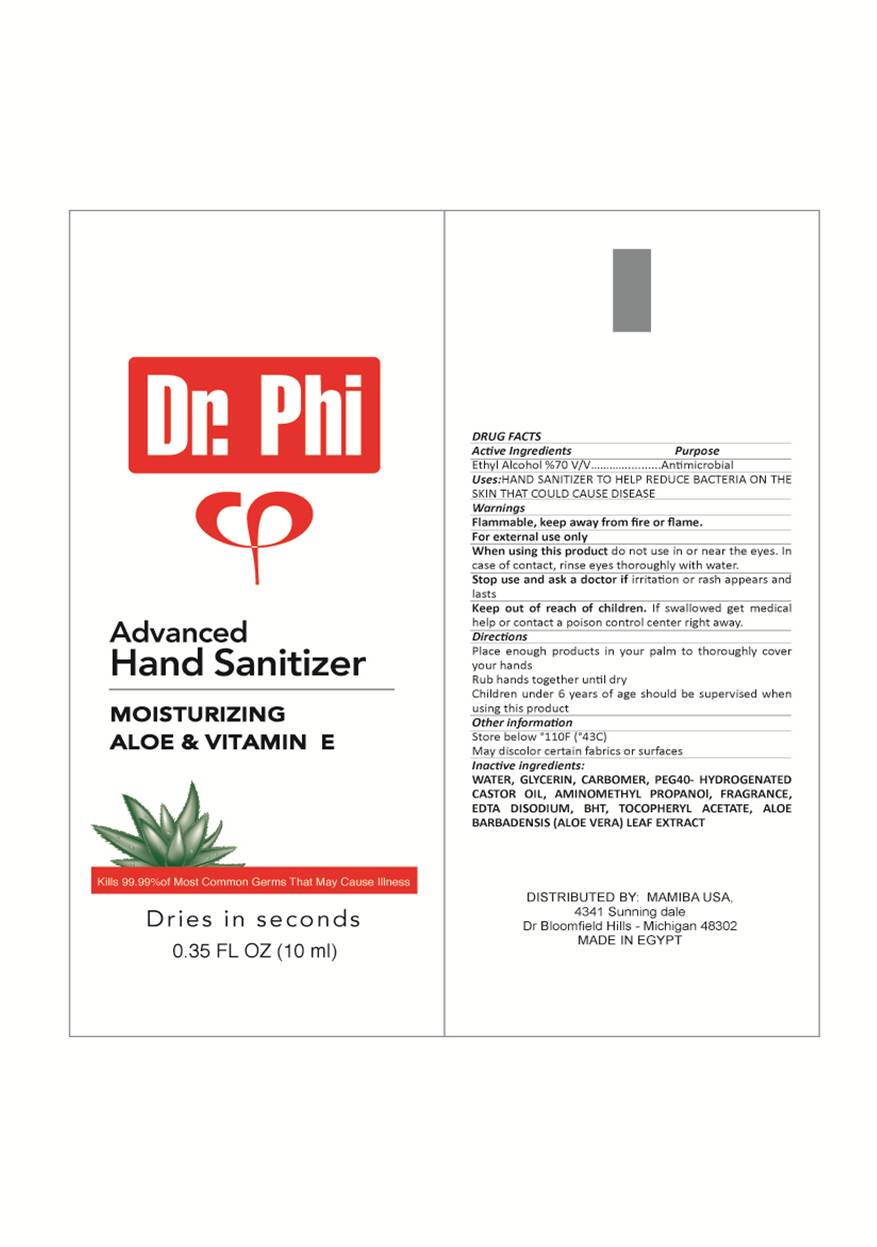 DRUG LABEL: Dr.Phi Advanced Hand sanitizer
NDC: 58161-156 | Form: GEL
Manufacturer: MAMIBA
Category: otc | Type: HUMAN OTC DRUG LABEL
Date: 20160526

ACTIVE INGREDIENTS: ALCOHOL 70 mL/100 mL
INACTIVE INGREDIENTS: WATER; GLYCERIN; CARBOMER 940; POLYOXYL 40 CASTOR OIL; AMINOMETHYLPROPANOL; EDETATE DISODIUM; BUTYLATED HYDROXYTOLUENE; ALPHA-TOCOPHEROL ACETATE; ALOE VERA LEAF POLYSACCHARIDES

Dr.Phi advanced hand sanitizer

active ingredient

ethyl alcohol % 70 V/V

purpose

antimicrobial

uses

hand sanitizer to help reduce bacteria on the skin that could cause disease

INDICATIONS AND USAGE

hand sanitizer to help reduce bacteria on the skin that could cause disease

warning

flamable , keep away from fire or flame

for external use only

keep out of reach of children

if swallowed get medical help or contact a poison control centre right away

when using this product

do not use in or near the eyes , in case of contact rinse eyes thoroughly with water

stop use and ask a doctor if

irritation and rash appears and lasts

directions

place enough prduct on your palm to thoroughly cover your hands

rub hands together until dry

other information

store below 110°F

may discolor certian fabrics or surfaces

inactive ingredients

water , glycerin , carbomer , PEG-40 hydrogentated castor oil , aminomethyl propanol, fragrance , EDTA disodium, BHT, tocopheryl acetate , aloe barbadensis (aloe vera) leaf extract.